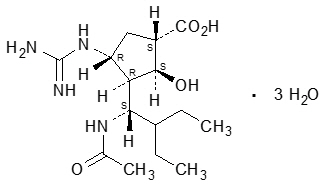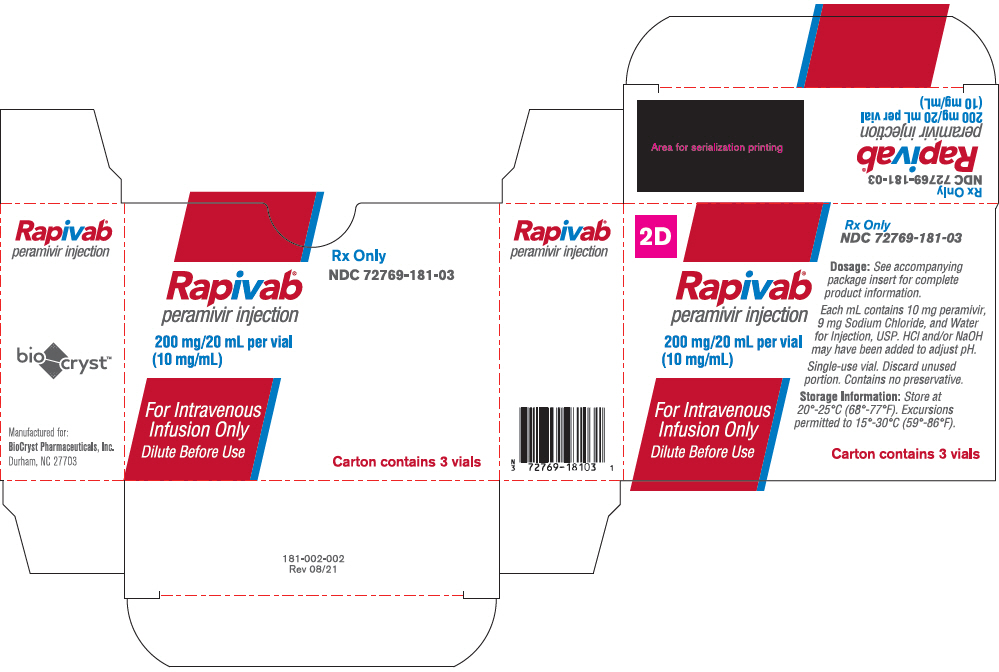 DRUG LABEL: Rapivab
NDC: 72769-181 | Form: SOLUTION
Manufacturer: BioCryst Pharmaceuticals, Inc.
Category: prescription | Type: HUMAN PRESCRIPTION DRUG LABEL
Date: 20240618

ACTIVE INGREDIENTS: Peramivir 600 mg/60 mL
INACTIVE INGREDIENTS: Sodium Chloride; Hydrochloric Acid; Sodium Hydroxide; Water

HIGHLIGHTS OF PRESCRIBING INFORMATION

These highlights do not include all the information needed to use RAPIVAB safely and effectively. See full prescribing information for RAPIVAB.
RAPIVAB® (peramivir) injection, for intravenous use
Initial U.S. Approval: 2014

1 INDICATIONS AND USAGE

RAPIVAB is an influenza virus neuraminidase inhibitor indicated for the treatment of acute uncomplicated influenza in patients 6 months and older who have been symptomatic for no more than two days. (1)

Limitations of Use:

- Efficacy based on clinical trials in which the predominant influenza virus type was influenza A; a limited number of subjects infected with influenza B virus were enrolled. (1)
- Consider available information on influenza drug susceptibility patterns and treatment effects when deciding whether to use. (1)
- Efficacy could not be established in patients with serious influenza requiring hospitalization. (1)

2 DOSAGE AND ADMINISTRATION

- Administer RAPIVAB as a single dose within 2 days of onset of influenza symptoms (2.1)
- Administer RAPIVAB by intravenous infusion for a minimum of 15 minutes (2.1)
  Recommended Dosage | Single Dose
  Adults and adolescents (13 years and older) | 600 mg
  Pediatric patients (6 months to 12 years of age) | 12 mg/kg (up to 600 mg)
  Recommended Dosage Adjustments in Patients with Altered Creatinine Clearance | Creatinine Clearance (mL/min)
  Recommended Dosage Adjustments in Patients with Altered Creatinine Clearance | ≥50 | 30-49 | 10-29
  Adults and adolescents (13 years and older) | 600 mg | 200 mg | 100 mg
  Pediatric patientsa (2 to 12 years of age) | 12 mg/kg | 4 mg/kg | 2 mg/kg
  a Up to maximum dose of 600 mg.
- No recommendation for dosage adjustment can be made for pediatric patients 6 months to less than 2 years of age with creatinine clearance less than 50 mL/min (2.2)
- Hemodialysis: Administer after dialysis (2.2)
- RAPIVAB must be diluted prior to administration (2.3)
- See the Full Prescribing Information for drug compatibility information (2.4)

3 DOSAGE FORMS AND STRENGTHS

Injection: 200 mg in 20 mL (10 mg/mL) in a single-use vial (3)

4 CONTRAINDICATIONS

Patients with known serious hypersensitivity or anaphylaxis to peramivir or any component of RAPIVAB (4)

5 WARNINGS AND PRECAUTIONS

- Cases of anaphylaxis and serious skin/hypersensitivity reactions such as Stevens-Johnson syndrome and erythema multiforme have occurred with RAPIVAB. Discontinue RAPIVAB and initiate appropriate treatment if anaphylaxis or serious skin reaction occurs or is suspected. (5.1)
- Neuropsychiatric events: Patients with influenza may be at an increased risk of hallucinations, delirium, and abnormal behavior early in their illness. Monitor for signs of abnormal behavior. (5.2)

6 ADVERSE REACTIONS

Most common adverse reaction (incidence >2%) is diarrhea. (6)

To report SUSPECTED ADVERSE REACTIONS, contact BioCryst Pharmaceuticals, Inc. at 1-833-633-2279 or FDA at 1-800-FDA-1088 or www.fda.gov/medwatch

7 DRUG INTERACTIONS

Live attenuated influenza vaccine (LAIV), intranasal: Avoid use of LAIV within 2 weeks before or 48 hours after administration of RAPIVAB, unless medically indicated (7.1)

FULL PRESCRIBING INFORMATION

1 INDICATIONS AND USAGE

RAPIVAB is indicated for the treatment of acute uncomplicated influenza in patients 6 months and older who have been symptomatic for no more than 2 days.

Limitations of Use:

- Efficacy of RAPIVAB is based on clinical trials of naturally occurring influenza in which the predominant influenza infections were influenza A virus; a limited number of subjects infected with influenza B virus were enrolled.
- Influenza viruses change over time. Emergence of resistance substitutions could decrease drug effectiveness. Other factors (for example, changes in viral virulence) might also diminish clinical benefit of antiviral drugs. Prescribers should consider available information on influenza drug susceptibility patterns and treatment effects when deciding whether to use RAPIVAB [see Microbiology (12.4)].
- The efficacy of RAPIVAB could not be established in patients with serious influenza requiring hospitalization [see Clinical Studies (14.3)].

2 DOSAGE AND ADMINISTRATION

2.1 Dosage in Acute Uncomplicated Influenza

Administer RAPIVAB within 2 days of onset of symptoms of influenza.

Adults and Adolescents (13 years of age and older)

The recommended dosage of RAPIVAB in adult and adolescent patients 13 years of age and older with acute uncomplicated influenza is a single 600 mg dose, administered via intravenous infusion for 15 to 30 minutes.

Pediatric Patients (6 months to 12 years of age)

The recommended dosage of RAPIVAB in pediatric patients 6 months to 12 years of age with acute uncomplicated influenza is a single 12 mg/kg dose (up to a maximum dose of 600 mg), administered via intravenous infusion for 15 to 30 minutes.

2.2 Dosing in Patients with Renal Impairment

Significantly increased drug exposures were observed when RAPIVAB was administered to adult subjects with renal dysfunction [see Clinical Pharmacology (12.3)]. Therefore, the RAPIVAB dosage should be reduced for patients with baseline creatinine clearance below 50 mL/min using the recommendations in Table 1 and Table 2. No dosage adjustment is required for single administration of RAPIVAB in patients with creatinine clearance of 50 mL/min or higher [see Clinical Pharmacology (12.3)].

In patients with chronic renal impairment maintained on hemodialysis, RAPIVAB should be administered after dialysis at a dose adjusted based on renal function (Table 1 and Table 2) [see Clinical Pharmacology (12.3)].

Table 1. Dosage Adjustment for Adults and Adolescents (13 Years and Older) with Altered Creatinine Clearance
 | Creatinine Clearancea (mL/min)
 | ≥50 | 30 to 49 | 10 to 29
Recommended Dose (mg) | 600 mg | 200 mg | 100 mg
a Calculated using the Cockcroft and Gault equation.

Table 2. Dosage Adjustment for Pediatric Patients (2 to 12 Years of Age) with Altered Creatinine Clearance
 | Creatinine Clearancea (mL/min)
 | ≥50 | 30 to 49 | 10 to 29
Recommended Dose (mg/kg)b | 12 mg/kg | 4 mg/kg | 2 mg/kg
a Calculated using the Cockcroft and Gault equation.
b Up to maximum dose of 600 mg.

No data are available to inform a recommendation for dosage adjustment with RAPIVAB in pediatric patients 6 months to less than 2 years of age with creatinine clearance less than 50 mL/min [see Use in Specific Populations (8.4, 8.6), Clinical Pharmacology (12.3)].

2.3 Preparation of RAPIVAB for Intravenous Infusion

Use aseptic technique during the preparation of RAPIVAB to prevent inadvertent microbial contamination. There is no preservative or bacteriostatic agent present in the solution.

Follow the steps below to prepare a diluted solution of RAPIVAB:

(a) Do not use if seal over bottle opening is broken or missing.
(b) Visually inspect RAPIVAB for particulate matter and discoloration prior to administration.
(c) Dilute an appropriate dose of RAPIVAB 10 mg/mL solution [see Dosage and Administration (2.1, 2.2)] in 0.9% or 0.45% sodium chloride, 5% dextrose, or lactated Ringer's. The maximum infusion volume is provided in Table 3. The final concentration of diluted RAPIVAB for administration should be between 1 mg/mL and 6 mg/mL.
  Table 3. Maximum Infusion Volume by Age and Weight
  Age | Weight (kg) | Maximum Infusion Volumea (mL)
  Infants 6 months to 1 year of age | Any | 25 mL
  Adults and pediatric patients 1 year and older | 5 kg to less than 10 kg | 25 mL
  Adults and pediatric patients 1 year and older | 10 kg to less than 15 kg | 50 mL
  Adults and pediatric patients 1 year and older | 15 kg to less than 20 kg | 75 mL
  Adults and pediatric patients 1 year and older | At least 20 kg | 100 mL
  aInfusion volume is the total volume of RAPIVAB 10 mg/mL solution and diluent. The final concentration of diluted RAPIVAB for administration should be between 1 mg/mL and 6 mg/mL.
(d) Administer the diluted solution via intravenous infusion for 15 to 30 minutes.
(e) Discard any unused diluted solution of RAPIVAB after 24 hours.

Once a diluted solution of RAPIVAB has been prepared, administer immediately or store under refrigerated conditions (2° to 8°C or 36° to 46°F) for up to 24 hours. If refrigerated, allow the diluted solution of RAPIVAB to reach room temperature then administer immediately.

2.4 Drug Compatibility

RAPIVAB injection is compatible with 0.9% or 0.45% sodium chloride, 5% dextrose, or lactated Ringer's. Do not mix or co-infuse RAPIVAB with other intravenous medications.

RAPIVAB injection is compatible with materials commonly used for administration such as polyvinylchloride (PVC) bags and PVC-free bags, polypropylene syringes, and polyethylene tubing.

3 DOSAGE FORMS AND STRENGTHS

Each vial of RAPIVAB injection contains 200 mg per 20 mL (10 mg per mL) as a clear, colorless solution [see How Supplied/Storage and Handling (16)].

4 CONTRAINDICATIONS

RAPIVAB is contraindicated in patients with known serious hypersensitivity or anaphylaxis to peramivir or any component of the product. Severe allergic reactions have included anaphylaxis, erythema multiforme, and Stevens-Johnson syndrome [see Warnings and Precautions (5.1)].

5 WARNINGS AND PRECAUTIONS

5.1 Serious Skin/Hypersensitivity Reactions

Rare cases of serious skin reactions, including erythema multiforme, have been reported with RAPIVAB in clinical studies and in postmarketing experience. Cases of anaphylaxis and Stevens-Johnson syndrome have been reported in postmarketing experience with RAPIVAB. Discontinue RAPIVAB and institute appropriate treatment if anaphylaxis or a serious skin reaction occurs or is suspected. The use of RAPIVAB is contraindicated in patients with known serious hypersensitivity or anaphylaxis to RAPIVAB [see Contraindications (4), Adverse Reactions (6.2)].

5.2 Neuropsychiatric Events

Influenza can be associated with a variety of neurologic and behavioral symptoms that can include events such as hallucinations, delirium, and abnormal behavior, in some cases resulting in fatal outcomes. These events may occur in the setting of encephalitis or encephalopathy but can occur in uncomplicated influenza as well.

There have been postmarketing reports of delirium and abnormal behavior leading to injury in patients with influenza who were receiving neuraminidase inhibitors, including RAPIVAB. Because these events were reported voluntarily during clinical practice, estimates of frequency cannot be made, but they appear to be uncommon. These events were reported primarily among pediatric patients and often had an abrupt onset and rapid resolution. The contribution of RAPIVAB to these events has not been established. Patients with influenza should be closely monitored for signs of abnormal behavior.

5.3 Risk of Bacterial Infections

There is no evidence for efficacy of RAPIVAB in any illness caused by agents other than influenza viruses. Serious bacterial infections may begin with influenza-like symptoms or may coexist with or occur as complications during the course of influenza. RAPIVAB has not been shown to prevent such complications.

Prescribers should be alert to the potential for secondary bacterial infections and treat with antibiotics as appropriate.

6 ADVERSE REACTIONS

The following adverse reactions are discussed in other sections of the labeling:

- Serious skin and hypersensitivity reactions [see Warnings and Precautions (5.1)]
- Neuropsychiatric events [see Warnings and Precautions (5.2)]

6.1 Clinical Trials Experience

Because clinical trials are conducted under widely varying conditions, adverse reaction rates observed in the clinical trials of a drug cannot be directly compared to rates in the clinical trials of another drug and may not reflect the rates observed in practice.

Adverse Reactions in Adults (18 years of age and older)

In 5 randomized, double-blind, controlled trials, 1,399 subjects with acute uncomplicated influenza received a single dose of RAPIVAB, administered intravenously or intramuscularly, at doses up to 600 mg. Among the 664 subjects receiving RAPIVAB 600 mg (intravenous or intramuscular), the most commonly observed adverse reaction was diarrhea, occurring at a rate of 8% versus 7% in subjects receiving placebo. No subject receiving RAPIVAB 600 mg experienced a serious adverse event and <1% discontinued study because of an adverse reaction.

Clinically significant laboratory abnormalities (DAIDS Grades 2 to 4) listed in Table 4 occurred more frequently in subjects treated with RAPIVAB 600 mg (intravenous or intramuscular) than placebo. Only events occurring at ≥2% are included.

Table 4: Laboratory Abnormalities Occurring in ≥2% of Subjects Treated with RAPIVAB 600 mg
Laboratory Parameter Abnormalitya | RAPIVAB 600 mg | Placebo
Alanine Aminotransferase (>2.5 × ULN) | (n = 654) 3% | (n = 430) 2%
Serum Glucose (>160 mg/dL) | (n = 660) 5% | (n = 433) 3%
Creatine Phosphokinase (≥6.0 × ULN) | (n = 654) 4% | (n = 431) 2%
Neutrophils (<1.000 ×10^9/L) | (n = 654) 8% | (n = 430) 6%
a Frequencies based on treatment-emergent laboratory abnormalities.

In a subset of subjects with serious influenza requiring hospitalization treated with RAPIVAB 600 mg as monotherapy (n = 101), the following adverse reactions were also reported more frequently with RAPIVAB as compared to placebo: constipation (4% versus 2%), insomnia (3% versus 0%), AST increased (3% versus 2%), and hypertension (2% versus 0%).

Adverse Reactions in Adolescent and Pediatric Subjects (6 months to 17 years of age)

Assessment of adverse reactions is based on a randomized, active-controlled study in which 130 adolescent and pediatric subjects ages 6 months to 17 years of age with acute uncomplicated influenza received open-label treatment with a single dose of RAPIVAB (n = 107), or 5 days of treatment with oseltamivir (n = 23) [see Use in Specific Populations (8.4), Clinical Studies (14.2)].

The safety profile of RAPIVAB in subjects 6 months to 17 years of age was generally similar to that observed in adults. The only adverse reaction reported in pediatric subjects treated with RAPIVAB (occurring in ≥2% of subjects) and not reported in adults was vomiting (3% versus 9% for oseltamivir). The only clinically significant laboratory abnormality (DAIDS Grade 2) occurring in ≥2% of pediatric subjects treated with RAPIVAB (and not previously reported in adults) was proteinuria by dipstick analysis (3% versus 0% for oseltamivir).

6.2 Postmarketing Experience

The following additional adverse reactions have been identified during postapproval use of RAPIVAB. Because postmarketing reactions are reported voluntarily from a population of uncertain size, it is not always possible to reliably estimate their frequency or establish a causal relationship to drug exposure.

Dermatologic: Stevens-Johnson syndrome, exfoliative dermatitis, rash [see Warnings and Precautions (5.1)].

General Disorders and Administration Site Conditions: Anaphylactic/anaphylactoid reactions [see Warnings and Precautions (5.1)].

Psychiatric: Abnormal behavior, hallucination [see Warnings and Precautions (5.2)].

7 DRUG INTERACTIONS

This section describes clinically relevant drug interactions with RAPIVAB. Drug-drug interaction studies are described elsewhere in the labeling [see Clinical Pharmacology (12.3)].

7.1 Influenza Vaccines

Inactivated influenza vaccine can be administered at any time relative to use of RAPIVAB. For live attenuated influenza vaccine (LAIV), antiviral drugs may inhibit viral replication and thus may reduce vaccine efficacy. The concurrent use of RAPIVAB with LAIV intranasal has not been evaluated. Because of the potential for interference between these two products, avoid use of LAIV within 2 weeks before or 48 hours after administration of RAPIVAB unless medically indicated.

8 USE IN SPECIFIC POPULATIONS

8.1 Pregnancy

Risk Summary

Limited available data with RAPIVAB use in pregnant women are insufficient to determine a drug-associated risk of adverse developmental outcomes. There are risks to the mother and fetus associated with influenza in pregnancy [see Clinical Considerations]. In animal reproduction studies, no adverse developmental effects were observed in rats when peramivir was administered by intravenous bolus injection during organogenesis at the maximum feasible dose, resulting in systemic drug exposures (AUC) approximately 8 times those in humans at the recommended dose. However, when peramivir was administered to rats by continuous intravenous infusion during the same gestation period, fetal abnormalities of reduced renal papilla and dilated ureters were observed. In rabbits, administration of peramivir during organogenesis at exposures 8 times those in humans at the recommended dose resulted in developmental toxicity (abortion or premature delivery) at a maternally toxic dose [see Data].

The estimated background risk of major birth defects and miscarriage for the indicated population is unknown. All pregnancies have a background risk of birth defect, loss, or other adverse outcomes. In the U.S. general population, the estimated background risk of major birth defects and miscarriage in clinically recognized pregnancies is 2% to 4% and 15% to 20%, respectively.

Clinical Considerations

Disease-Associated Maternal and/or Embryo/Fetal Risk

Pregnant women are at higher risk of severe complications from influenza, which may lead to adverse pregnancy and/or fetal outcomes including maternal death, stillbirths, birth defects, preterm delivery, low birthweight, and small for gestational age.

Data

Animal Data

Reproductive toxicity studies have been performed in rats and rabbits. In rats, peramivir was administered once daily by intravenous bolus injection at doses of 200, 400, and 600 mg/kg/day on Gestational Days 6 to 17. No treatment-related fetal toxicities were observed when peramivir was administered by intravenous bolus injection at the maximum feasible dose of 600 mg/kg, resulting in exposures approximately 8 times those in humans at the recommended dose.

Peramivir was also administered by continuous intravenous infusion to rats at daily doses of 50, 400, and 1000 mg/kg/day on Gestational Days 6 to 17. Dose related increases in the incidence of fetal abnormalities of reduced renal papilla and dilated ureters were observed at 400 and 1000 mg/kg/day. The systemic drug exposure in rats at a dose without fetal effects was less than the exposures in humans at the recommended dose.

In rabbits, peramivir was administered once daily by intravenous bolus injection at doses of 25, 50, 100, and 200 mg/kg/day on Gestational Days 7 to 19. Developmental toxicity (abortion or premature delivery) was observed at maternally toxic dose levels (100 and 200 mg/kg/day) resulting in exposures approximately 8 times those in humans at the recommended dose. The exposure in rabbits at doses without developmental toxicity was less than the exposure in humans at the recommended dose.

A pre/post-natal developmental toxicity study was performed in pregnant rats administered peramivir once daily by intravenous infusion at doses of 50, 200, 400, and 600 mg/kg/day on Gestational Day 6 through Lactation Day 20. No significant effects of peramivir on developmental outcomes were observed in nursing pups at up to the highest dose tested.

8.2 Lactation

Risk Summary

There are no data on the presence of RAPIVAB in human milk, the effects on the breastfed infant, or the effects on milk production. Peramivir is present in rat milk [see Data]. Limited clinical data during lactation preclude a clear determination of the risk of RAPIVAB to an infant during lactation; therefore, the developmental and health benefits of breastfeeding should be considered along with the mother's clinical need for RAPIVAB and any potential adverse effects on the breastfed child from the drug or from the underlying maternal condition.

Data

A pharmacokinetic study was performed in lactating rats administered a single intravenous dose of peramivir (10 mg/kg) on Lactation/Postpartum Days 11 to 13. The maximum concentration of peramivir in milk was reached at 0.75 hours post-dose. The milk to plasma AUC ratio of peramivir was approximately 0.5.

8.4 Pediatric Use

The safety and effectiveness of RAPIVAB for the treatment of influenza has been established in pediatric patients 6 months to 17 years of age. Use of RAPIVAB for this indication is supported by evidence from adequate and well-controlled trials of RAPIVAB in adults with additional data from Study 305, a randomized, active-controlled trial of 130 adolescent and pediatric subjects with acute uncomplicated influenza who received open-label treatment with a single dose of RAPIVAB or 5 days of treatment with oseltamivir administered within 48 hours of onset of symptoms of influenza [see Dosage and Administration (2.1, 2.2, 2.3), Adverse Reactions (6.1), Clinical Pharmacology (12.3), Clinical Studies (14.2)]. Study 305 included:

- 13 to 17 years of age: 21 subjects treated with RAPIVAB 600 mg
- 6 months to 12 years of age: 86 subjects treated with RAPIVAB 12 mg/kg (up to a maximum dose of 600 mg)

Safety and effectiveness of RAPIVAB in pediatric patients less than 6 months of age have not been established. No data are available for RAPIVAB use in pediatric patients 6 months to less than 2 years with creatinine clearance <50 mL/min to inform a recommendation for dosage adjustment [see Dosage and Administration (2.2), Clinical Pharmacology (12.3)].

8.5 Geriatric Use

Clinical trials of RAPIVAB did not include sufficient numbers of subjects aged 65 and over to determine whether they respond differently from younger subjects. Other reported clinical experience has not identified differences in exposures between the elderly and younger subjects [see Clinical Pharmacology (12.3)].

8.6 Patients with Impaired Renal Function

A reduced dose of RAPIVAB is recommended for patients 2 years and older with creatinine clearance <50 mL/min [see Dosage and Administration (2.2), Clinical Pharmacology (12.3)]. Dose adjustment is not required for a single administration of RAPIVAB for patients with creatinine clearance ≥50 mL/min [see Dosage and Administration (2.2), Clinical Pharmacology (12.3)].

In patients with chronic renal impairment maintained on hemodialysis, RAPIVAB should be administered after dialysis at a dose adjusted based on renal function [see Dosage and Administration (2.2), Clinical Pharmacology (12.3)].

No data are available for RAPIVAB use in pediatric patients 6 months to less than 2 years with creatinine clearance <50 mL/min to inform a recommendation for dosage adjustment [see Dosage and Administration (2.2), Clinical Pharmacology (12.3)].

8.7 Patients with Serious Influenza Requiring Hospitalization

The use of RAPIVAB was not shown to provide benefit in patients with serious influenza requiring hospitalization [see Indications and Usage (1), Clinical Studies (14.2)].

10 OVERDOSAGE

There is no human experience of acute overdosage with RAPIVAB. Treatment of overdosage with RAPIVAB should consist of general supportive measures including monitoring of vital signs and observation of the clinical status of the patient. There is no specific antidote for overdose with RAPIVAB.

RAPIVAB is cleared by renal excretion and can be cleared by hemodialysis.

11 DESCRIPTION

RAPIVAB (peramivir) is an inhibitor of influenza virus neuraminidase. The chemical name is (1S,2S,3R,4R)-3-[(1S)-1-(acetylamino)-2-ethylbutyl]-4-(carbamimidoylamino)-2-hydroxycyclopentanecarboxylic acid, trihydrate. The chemical formula is C15H28N4O4 ∙ 3H2O, representing a molecular weight of 382.45. The molecular structure is as follows:

RAPIVAB injection is a clear, colorless, sterile, isotonic solution (200 mg per 20 mL) in glass vials fitted with rubber stoppers and royal blue flip-off seals. Each mL contains 10 mg peramivir (on an anhydrous basis) in 0.9% sodium chloride solution. The pH may have been adjusted with sodium hydroxide, USP and/or hydrochloric acid, USP. The pH is 5.5 to 8.5.

12 CLINICAL PHARMACOLOGY

12.1 Mechanism of Action

Peramivir is an antiviral drug with activity against influenza virus [see Microbiology (12.4)].

12.2 Cardiac Electrophysiology

At twice the maximum recommended dose, RAPIVAB did not prolong the QTc interval to any clinically relevant extent.

12.3 Pharmacokinetics

The pharmacokinetics of RAPIVAB was evaluated in Phase 1 trials in adults. The pharmacokinetic parameters following intravenous administration of RAPIVAB (0.17 to 2 times the recommended dose) showed a linear relationship between dose and exposure parameters (Cmax and AUC).

Following intravenous administration of a single dose of RAPIVAB 600 mg over 30 minutes, a maximum plasma concentration (Cmax) of 46,800 ng/mL (46.8 µg/mL) was reached at the end of infusion. AUC0-∞ values were 102,700 ng∙hr/mL.

Distribution

In vitro binding of peramivir to human plasma proteins is <30%.

Based on a population pharmacokinetic analysis, the central volume of distribution was 12.56 L.

Metabolism and Elimination

Peramivir is not a substrate for cytochrome P450 (CYP) enzymes, does not affect glucuronidation, and is not a substrate or inhibitor of P-glycoprotein mediated transport.

Peramivir is not significantly metabolized in humans.

The elimination half-life of RAPIVAB following intravenous administration to healthy subjects of 600 mg as a single dose is approximately 20 hours. The major route of elimination of RAPIVAB is via the kidney. Renal clearance of unchanged peramivir accounts for approximately 90% of total clearance. Negligible accumulation was observed following multiple doses, either once or twice daily, for up to 10 days.

Specific Populations

Race: Pharmacokinetics of peramivir was evaluated primarily in Caucasians and Asians. Based on a population pharmacokinetic analysis including race as a covariate, volume of distribution was dependent on weight and Asian race. No dose adjustment is required based on weight or Asian race.

Gender: Peramivir pharmacokinetics was similar in male and female subjects.

Pediatric Patients: The pharmacokinetics of peramivir has been evaluated in a study in pediatric subjects 6 months to 17 years of age with acute uncomplicated influenza. Pharmacokinetic sampling in this study was limited to approximately 3 hours after administration of peramivir. Geometric mean (GM) PK parameters are provided in Table 5.

Table 5. Geometric Mean (%CV) Cmax and AUC0-3 by Age Group in Comparison to Adults
Age Group | GM Cmax (ng/mL) (%CV) | GM AUC0-3 (ng.h/mL) (%CV)
6 months to <2 years | 38,000 (73.7) | 46,200 (35.8)
2 to <7 years | 47,400 (48.4) | 62,700 (39.7)
7 to <13 years | 61,200 (53) | 76,300 (43.1)
13 to <18 years | 51,500 (33) | 65,500 (28.1)
Healthy Adults (Study 113) | 45,700 (21.5) | 68,500 (19.1)

Peramivir pharmacokinetics in subjects 2 to 17 years of age was similar to adults. In pediatric patients 6 months to less than 2 years of age, the GM AUC0-3 and Cmax were lower than that of healthy adult subjects, with GM ratios (90% CI) of 0.68 (0.52 to 0.88) and 0.83 (0.59 to 1.18), respectively. The difference in exposure is not considered to be clinically significant.

Geriatric Patients: Peramivir pharmacokinetics in elderly subjects was similar to non-elderly subjects. Peak concentrations of peramivir after a single 4 mg/kg intravenous dose were approximately 10% higher in elderly subjects when compared to young adults (22,647 vs 20,490 ng/mL, respectively). Exposure (AUC0-12) to peramivir at steady state was roughly 34% higher in elderly subjects compared to young adults (61,572 vs 46,000 ng∙hr/mL, respectively). Dose adjustment is not required for elderly patients.

Patients with Impaired Renal Function: A trial was conducted in adult subjects with various degrees of renal impairment. When compared to a concurrent cohort with normal renal function, no change in mean Cmax was observed (6 subjects per cohort). However, mean AUC0-∞ after a single 2 mg/kg intravenous dose was increased by 28%, by 302%, and by 412% in subjects with creatinine clearance 50 to 79, 30 to 49, and 10 to 29 mL/min, respectively.

Hemodialysis was effective in reducing systemic exposure of peramivir by 73% to 81%.

A reduced dose of RAPIVAB is recommended for adult and adolescent patients 13 years and older with creatinine clearance <50 mL/min [see Dosage and Administration (2.2)].

The pharmacokinetics of peramivir has not been studied in pediatric subjects with renal impairment. Given that the pharmacokinetics in pediatric subjects with normal renal function is comparable to that observed in adults, the same proportional dose reduction is recommended in pediatric patients with renal impairment >2 years of age [see Dosage and Administration (2.2)].

In pediatric patients with renal impairment less than 2 years of age, given the developmental immaturity of renal function in this age group, a recommendation for dose reduction cannot be made [see Dosage and Administration (2.2)].

Patients with Hepatic Impairment: The pharmacokinetics of peramivir in subjects with hepatic impairment has not been studied. No clinically relevant alterations to peramivir pharmacokinetics are expected in patients with hepatic impairment based on the route of peramivir elimination.

Assessment of Drug Interactions

The potential for CYP-mediated interactions involving RAPIVAB with other drugs is low, based on the known elimination pathway of RAPIVAB, and data from in vitro studies indicating RAPIVAB does not induce or inhibit CYP P450.

There was no evidence of drug-drug interactions when RAPIVAB was administered with oral rimantadine, oseltamivir, or oral contraceptives containing ethinyl estradiol and levonorgestrel; or when peramivir IM was administered with oral probenecid.

RAPIVAB is primarily cleared in the urine by glomerular filtration.

12.4 Microbiology

Mechanism of Action

Peramivir is an inhibitor of influenza virus neuraminidase, an enzyme that releases viral particles from the plasma membrane of infected cells. The median neuraminidase inhibitory activities (IC50 values) of peramivir in biochemical assays against influenza A/H1N1 virus, influenza A/H3N2 virus, and influenza B virus clinical isolates were 0.16 nM (n = 44; range: 0.01 to 1.77 nM), 0.13 nM (n = 32; range: 0.05 to 11 nM), and 0.99 nM (n = 39; range: 0.04 to 54.2 nM), respectively, in a neuraminidase assay with a fluorescently labeled MUNANA substrate.

Antiviral Activity

The antiviral activity of peramivir against laboratory strains and clinical isolates of influenza virus was determined in cell culture. The concentrations of peramivir required for inhibition of influenza virus in cell culture varied depending on the assay method used and the virus tested. The median 50% effective concentrations (EC50 values) of peramivir in cell culture assays were 2.6 nM (n = 13; range: 0.09 to 21 nM), 0.08 nM (n = 17; range: 0.01 to 1.9 nM) and 4.8 nM (n = 11; range: 0.06 to 120 nM) for influenza A/H1N1 virus, A/H3N2 virus, and B virus strains, respectively.

The relationship between the antiviral activity in cell culture, inhibitory activity in the neuraminidase assay, and the inhibition of influenza virus replication in humans has not been established.

Resistance

Cell culture: Influenza A and B virus isolates with reduced susceptibility to peramivir were recovered by serial passage of virus in cell culture in the presence of increasing concentrations of peramivir. Reduced susceptibility of influenza virus to inhibition by peramivir may be conferred by amino acid substitutions in the viral neuraminidase or hemagglutinin proteins (Table 6).

Table 6: Amino Acid Substitutions Selected by Peramivir in Cell Culture Studies
 | Influenza Virus Type/Subtype
Protein | A/H1N1a | A/H3N2b | Bc
HAd | D125S, R208K | N63K, G78D, N145D, K189E | T139N, G141E, R162M, D195N, T198N, Y319H
NA | N58D, I211T, H275Y | - | H273Y
a Numbering based on A/California/04/2009.
b Numbering based on A/Texas/50/2012.
c Numbering based on B/Massachusetts/02/2012.
d Numbering begins after the predicted signal peptide.

In vivo: Influenza A and B virus isolates with amino acid substitutions associated with reduced susceptibility to peramivir were observed in clinical isolates collected during clinical trials with peramivir (Table 7). Amino acid substitutions have also been observed in viral isolates sampled during community surveillance studies which may be associated with reduced susceptibility to peramivir (Table 7). The clinical impact of this reduced susceptibility is unknown and may be strain dependent.

Table 7: Neuraminidase and Hemagglutinin Amino Acid Substitutions Associated with Reduced Susceptibility to Peramivir in Clinical Virus Isolates
 |  | Influenza Virus Type / Subtype
Protein |  | A/H1N1a | A/H3N2b | Bc
NA | Clinical Trial | R152K, H275Y | R292K, N294S | -
NA | Community Surveillance Studies | G147R, I223R/V, S247N/R, H275Y, N295S, I427T | E119V, Q136K, V143M+S315R, D151A/E/G/N/Vd, V313A, Q391K | G104E, E105K, I115T, H134N/Y, P139S, G145E/R, D197E/N/Y, A200T, I221T/V, G243S, A245T, G247D+I361V, H273Y, N294S, K360E, R374K, A395E, D432G/N
HA | Clinical Trial | V479F | - | -
a Numbering based on A/California/04/2009.
b Numbering based on A/Texas/50/2012.
c Numbering based on B/Massachusetts/02/2012.
d Substitutions at this site may be potential cell culture artifacts.

Circulating seasonal influenza strains expressing neuraminidase resistance-associated substitutions have been observed in individuals who have not received RAPIVAB. Prescribers should consider available information from the CDC on influenza virus drug susceptibility patterns and treatment effects when deciding whether to use RAPIVAB.

Zoonotic Viruses: Amino acid substitutions have been observed in H5N1 and H7N9 clinical viral isolates that conferred reduced susceptibility to peramivir in neuraminidase biochemical assays (Table 8). The clinical impact of reduced susceptibility in these viruses is unknown, and the effects of specific substitutions on virus susceptibility to peramivir may be strain dependent.

Table 8. Amino Acid Substitutions Observed in Avian Influenza Viruses with Zoonotic Potential and Associated with Reduced Susceptibility to Peramivir
 | Influenza Virus Type/Subtype
Protein | A/H5N1a | A/H7N9b
NA | H275Y | R292K
a Numbering based on A/California/04/2009.
b Numbering based on A/Texas/50/2012.

Cross Resistance

Cross-resistance between peramivir, oseltamivir, and zanamivir was observed in neuraminidase biochemical assays and cell culture assays. The amino acid substitutions that resulted in reduced susceptibility to peramivir and either oseltamivir or zanamivir are summarized in Table 9. The clinical impact of this reduced susceptibility is unknown and may be strain dependent.

Table 9: Summary of Amino Acid Substitutions with Cross-Resistance between Peramivir and Oseltamivir or Zanamivir in Susceptibility Assays
 |  | Influenza Virus Type/Subtype
 | Protein | A/H1N1a | A/H3N2b | Bc
Oseltamivir | HAd | - | N63K, N145D | -
 | NA | E119D/V, D151G/N, R152K, Y155H, D199G, I223R/T/V, S247N, G249R+I267V, H275Y, N295S, Q313R, R368K, I427T | E119I/V, I222V, S247P, R292K, N294S, V313A | G104E, E105K, G108E, P139S, G140R, G145R, D197E/N/Y, A200T, I221T/V/L, G243S, A245T, H273Y, N294S, R374K, A395E, G407S
Zanamivir | HAd | - | N63K, N145D | -
 | NA | E119D/G, Q136Ke, R152K, Y155H, D199G, I223T, I223R+H275Y, S247N, G249R+I267V, N295S, Q313R, R368K, I427T | E119G/V, T148I, D151A/G/N/V, I222V, S247P, R292K, N294S | G104E, E105K, G108E, E117A/D/G, H134N, P139S, G145R, R150K, D197E/N/Y, A200T, I221T/L, G243S, A245T, G247D+I361V, R292K, R374K, G407S
a Numbering based on A/California/04/2009.
b Numbering based on A/Texas/50/2012.
c Numbering based on B/Massachusetts/02/2012.
d Numbering begins after the predicted signal peptide.
e Substitutions at this site may be potential cell culture artifacts.

Cross-resistance between neuraminidase (NA) inhibitors and M2 ion channel inhibitors (adamantanes), or between NA inhibitors and polymerase acidic (PA) endonuclease inhibitors (baloxavir), is not expected because these classes of drugs target different viral proteins. However, a virus may carry multiple substitutions that each confer resistance to a different inhibitor class and together can confer multi-class resistance. The clinical relevance of phenotypic cross-resistance evaluations has not been established and may be strain dependent.

Immune Response

No influenza vaccine/peramivir interaction study has been conducted.

13 NONCLINICAL TOXICOLOGY

13.1 Carcinogenesis, Mutagenesis, Impairment of Fertility

Carcinogenesis

Carcinogenicity studies by intravenous injection of peramivir were not performed. However, in an oral carcinogenicity study in Sprague-Dawley rats no drug-related neoplasms were observed at drug exposures 0.2- to 0.5-fold that of humans at the clinically recommended dose of 600 mg/day.

Mutagenesis

Peramivir was not mutagenic or clastogenic in a battery of in vitro and in vivo assays including the Ames bacterial reverse mutation assay, the Chinese hamster ovary chromosomal aberration test, and the in vivo mouse micronucleus test with intravenous administration.

Impairment of Fertility

Peramivir had no effects on mating or fertility in rats up to 600 mg/kg/day, at which exposures were approximately 8-fold of those in humans at the clinically recommended dose.

13.2 Animal Toxicology and/or Pharmacology

Peramivir caused renal tubular necrosis and abnormal renal function in rabbits. Toxicities included tubular dilatation and necrosis with protein casts in cortical areas, dilated tubules with mineralization in corticomedullary junction areas, and multifocal tubular regeneration. The rabbit appeared to be the sensitive species for peramivir renal toxicity, which was noted at exposures approximately 2- to 4-fold those in humans at the clinically recommended dose.

14 CLINICAL STUDIES

14.1 Acute Uncomplicated Influenza in Adults

Study 621 was a randomized, multicenter, blinded study conducted in Japan that evaluated a single intravenous administration of RAPIVAB 300 mg, RAPIVAB 600 mg, or placebo administered over 30 minutes in subjects 20 to 65 years of age with acute uncomplicated influenza. Subjects were eligible if they had fever ≥38°C (axillary) and a positive rapid antigen test for influenza virus, accompanied by at least 2 symptoms (cough, nasal symptoms, sore throat, myalgia, chills/sweats, malaise, fatigue, or headache). In addition, all subjects enrolled were allowed to take fever-reducing medications.

Study treatment was started within 48 hours of onset of symptoms. Subjects participating in the study were required to self-assess their influenza symptoms as "none", "mild", "moderate", or "severe" twice daily. The primary endpoint, time to alleviation of symptoms, was defined as the number of hours from initiation of study drug until the start of the 24-hour period in which all 7 symptoms of influenza (cough, sore throat, nasal congestion, headache, feverishness, myalgia, and fatigue) were either absent or present at a level no greater than mild for at least 21.5 hours.

The overall efficacy population, consisting of subjects with confirmed influenza and administered study drug, totaled 297 subjects. Among the 98 subjects enrolled in the RAPIVAB 600 mg dose group, the mean age was 34 years; 55% were male; 34% were smokers; 99% were infected with influenza A virus and 1% were infected with influenza B virus. The majority of subjects (53%) had influenza illness lasting <24 hours at the time of presentation.

Overall, subjects receiving RAPIVAB 600 mg experienced alleviation of their combined influenza symptoms a median of 21 hours sooner than those receiving placebo. The median time to recovery to normal temperature (<37°C) in the 600 mg group was approximately 12 hours sooner compared to placebo.

Insufficient numbers of subjects infected with influenza B virus were enrolled to determine efficacy of RAPIVAB in this influenza type.

14.2 Acute Uncomplicated Influenza in Pediatric Subjects

Study 305 was a randomized, multicenter, open-label, active-controlled trial to evaluate the safety, pharmacokinetics, and efficacy of a single intravenous dose of RAPIVAB administered for a minimum of 15 minutes in subjects 6 months to 17 years of age with acute uncomplicated influenza who had fever ≥37.8°C (oral) with at least one respiratory symptom (cough or rhinitis) or a positive influenza rapid antigen test. Study treatment was started within 48 hours of onset of symptoms. Subjects were randomized to receive RAPIVAB 600 mg (13 to 17 years of age), RAPIVAB 12 mg/kg up to a maximum dose of 600 mg (6 months to 12 years of age), or oral oseltamivir taken twice daily for 5 days. In addition, all enrolled subjects were allowed to take fever-reducing medications.

The overall efficacy population, consisting of subjects with confirmed influenza who were administered study drug, totaled 97 subjects. Among the 81 subjects treated with RAPIVAB, the median age was 7.5 years; 52% were male; 60% were infected with influenza A virus, 33% were infected with influenza B virus, and 6% were co-infected with influenza A and B viruses.

The primary endpoint was the safety of peramivir compared to oseltamivir as measured by adverse events, laboratory analysis, vital signs, and physical exams. Secondary endpoints included efficacy outcomes such as time to resolution of influenza symptoms and time to resolution of fever; however, the study was not powered to detect statistically significant differences in these secondary endpoints. Subjects receiving RAPIVAB experienced a median time to alleviation of their combined influenza symptoms of 79 hours (interquartile range: 31 to 126 hours) compared to 100 hours (interquartile range: 57 to 145 hours) in subjects receiving oseltamivir. The median time to recovery to normal temperature (<37°C) was 40 hours (interquartile range: 21 to 68 hours) and 35 hours (interquartile range: 16 to 42 hours) in subjects receiving RAPIVAB and oseltamivir, respectively [see Use in Specific Populations (8.4)].

14.3 Serious Influenza Requiring Hospitalization

The efficacy of RAPIVAB could not be established in patients with serious influenza requiring hospitalization [see Indications and Usage (1)].

A randomized, double-blind, multicenter, placebo-controlled trial (Study 301) was conducted in 398 subjects with serious influenza requiring hospitalization. Subjects were randomized to receive RAPIVAB 600 mg daily for 5 days plus standard of care versus standard of care plus placebo within 72 hours of start of symptoms. The primary endpoint was time to clinical resolution defined as the time in hours from initiation of study treatment until resolution of at least 4 of 5 signs (temperature, oxygen saturation, respiration rate, heart rate, or systolic blood pressure), maintained for at least 24 hours. RAPIVAB plus standard of care did not improve median time to clinical resolution compared with standard of care alone.

16 HOW SUPPLIED/STORAGE AND HANDLING

RAPIVAB injection is a clear, colorless sterile, isotonic solution. Each single-use vial contains 200 mg per 20 mL (10 mg/mL) of peramivir in a clear glass vial (NDC # 72769-181-01). RAPIVAB injection is supplied in cartons containing 3 single-use vials (NDC # 72769-181-03).

STORAGE AND HANDLING

Store vials of RAPIVAB injection in original cartons at 20°C to 25°C (68°F to 77°F). Excursions are permitted to 15°C to 30°C (59°F to 86°F).

Do not use if seal over bottle opening is broken or missing.

17 PATIENT COUNSELING INFORMATION

Advise patients of the following:

- There is a risk of severe allergic reactions (including anaphylaxis) or serious skin reactions with RAPIVAB use. Advise patients to seek immediate medical attention if an allergic-like reaction occurs or is suspected [see Warnings and Precautions (5.1)].
- There is a risk of neuropsychiatric events in patients with influenza. Patients should contact their physician if they experience signs of abnormal behavior after receiving RAPIVAB [see Warnings and Precautions (5.2)].

RAPIVAB is a registered trademark of BioCryst Pharmaceuticals, Inc.

Manufactured for and distributed by:
BioCryst Pharmaceuticals, Inc.
Durham, NC 27703

RAP:9PI

PRINCIPAL DISPLAY PANEL - 200 mg/20 mL Vial Carton

Rx Only

NDC 72769-181-03

Rapivab®
peramivir injection

200 mg/20 mL per vial
(10 mg/mL)

For Intravenous
Infusion Only
Dilute Before Use

Carton contains 3 vials